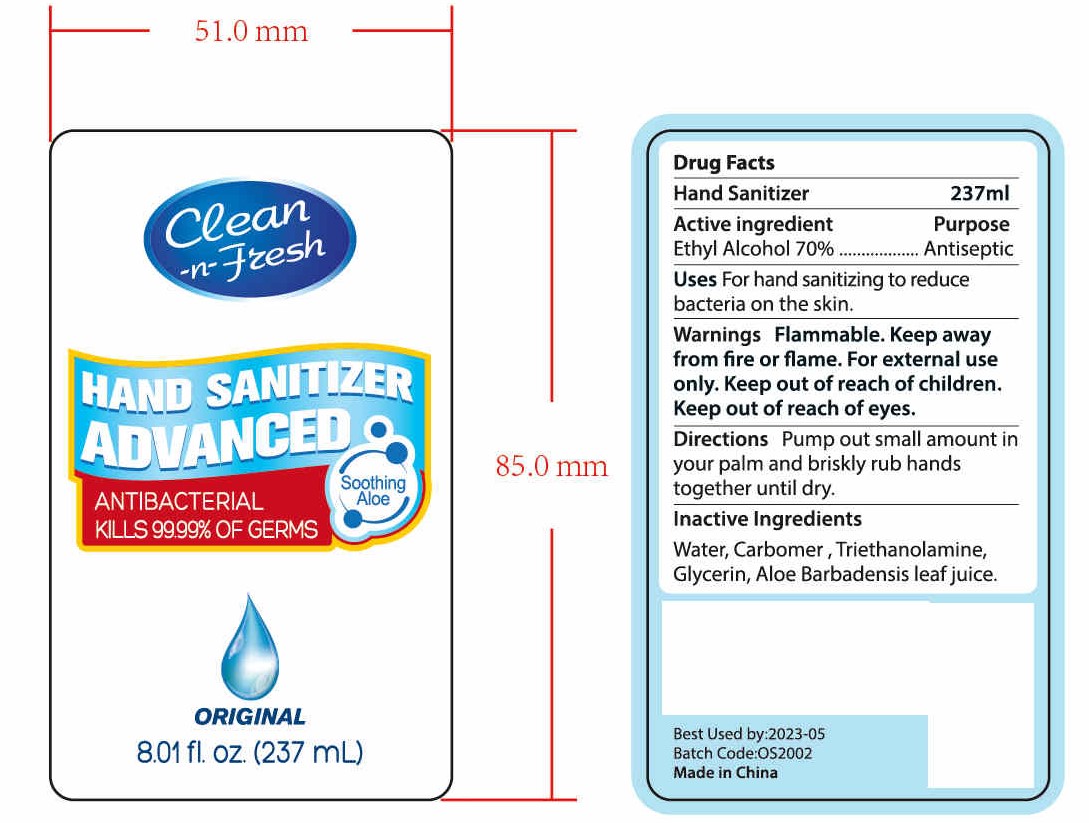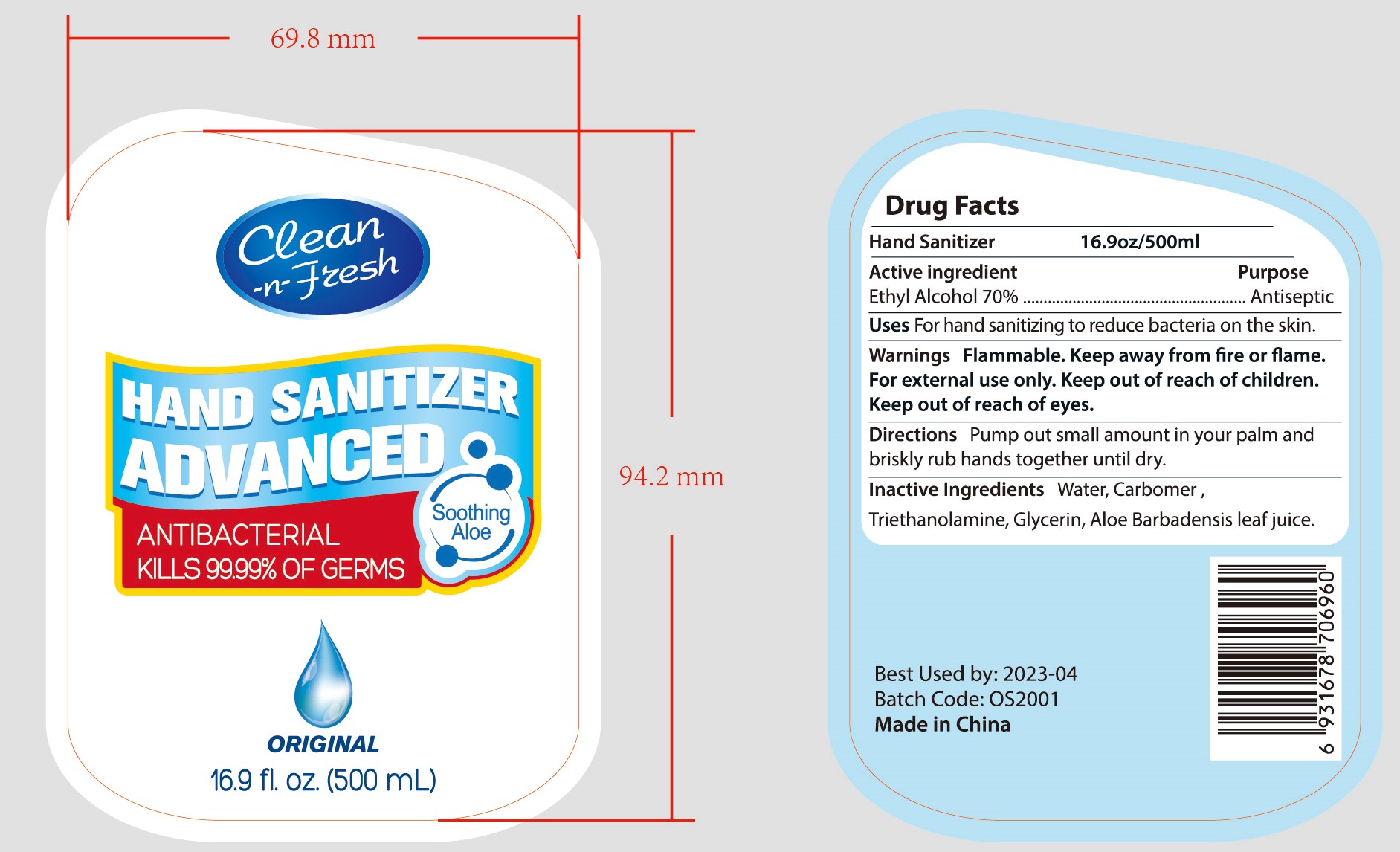 DRUG LABEL: HAND SANITIZER
NDC: 47993-214 | Form: GEL
Manufacturer: NINGBO JIANGBEI OCEAN STAR TRADING CO.,LTD
Category: otc | Type: HUMAN OTC DRUG LABEL
Date: 20201029

ACTIVE INGREDIENTS: ALCOHOL 70 g/112 mL
INACTIVE INGREDIENTS: WATER 12 g/112 mL; TRIETHANOLAMINE BENZOATE 3 g/112 mL; CARBOMER 940 12 g/112 mL; GLYCERIN 2 g/112 mL; ALOE VERA LEAF 1 g/112 mL

47993-214

Active ingredients

Ethyl Alcohol 70%

PURPOSE

Antiseptic

Uses:
For hand sanitizing to reduce bacteria on the skin.

Warnings:

Flammable: Keep away from fire or flame.For external use only.

Keep out of reach of children. Keep out of reach of eyes.

Directions:

Pump out small amount in your palm and briskly rub hands together until dry.

Inactive ingredients

Water，Carbomer ，Triethanolamine，Glycerin，Aloe Barbadensis leaf juice